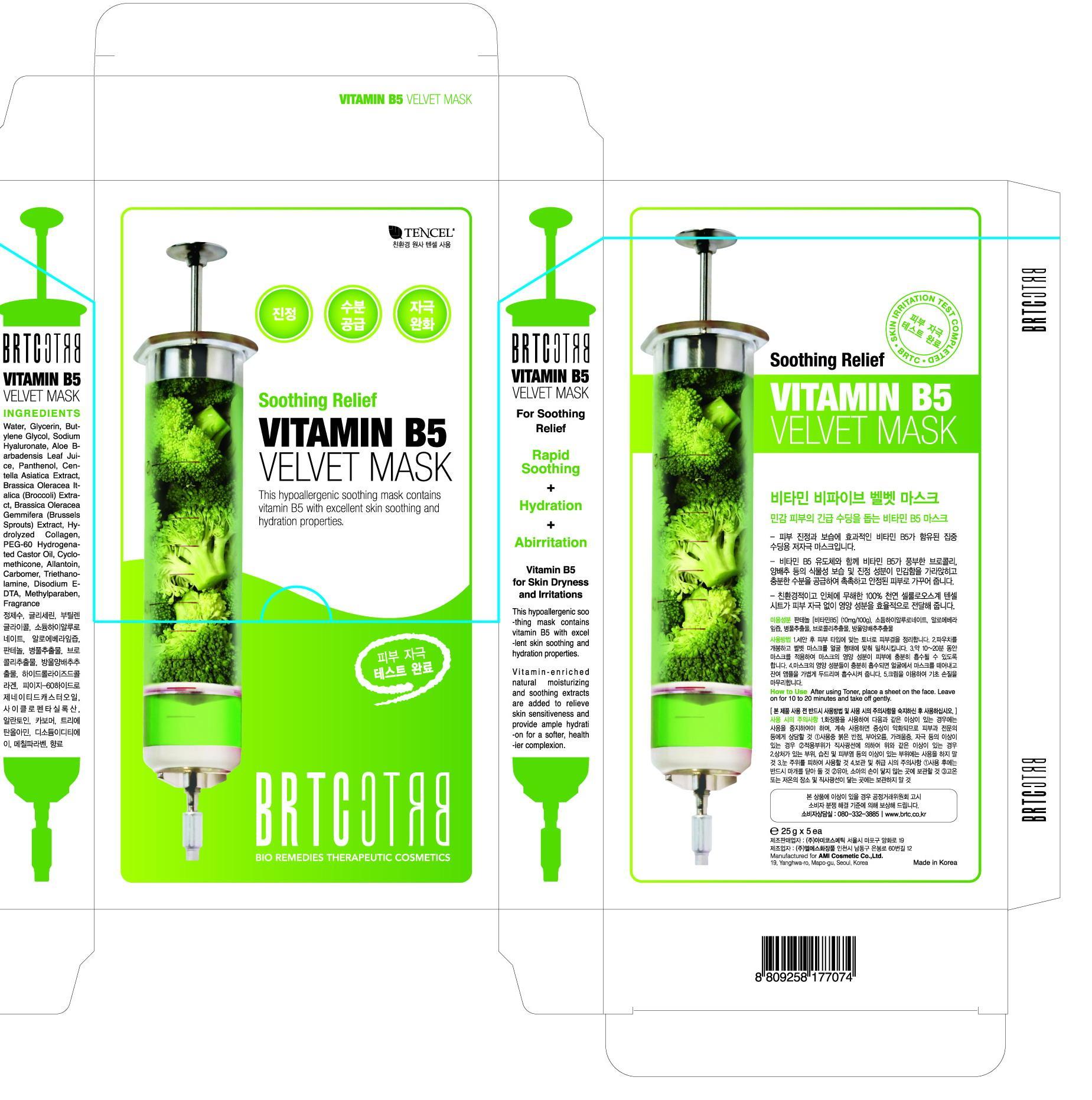 DRUG LABEL: Vitamin B5 Velvet Mask
NDC: 59535-9401 | Form: LIQUID
Manufacturer: AMI Cosmetic Co.,Ltd.
Category: otc | Type: HUMAN OTC DRUG LABEL
Date: 20190330

ACTIVE INGREDIENTS: GLYCERIN 0.06 g/1 g
INACTIVE INGREDIENTS: WATER; BUTYLENE GLYCOL; HYALURONATE SODIUM; PANTHENOL

Drug Facts

ACTIVE INGREDIENT

glycerin

INACTIVE INGREDIENT

water, butylene glycol, sodium hyaluronate, panthenol allantoin, carbomer, methylparaben, etc

PURPOSE

skin protectant

keep out of reach of the children

INDICATIONS AND USAGE

apply on the skin as needed

WARNINGS

・Stop using the product when you have skin problems or the product disagrees with your skin
・Stop using the product immediately and consult a dermatologist if you have redness, swelling, itching or irritation on the skin while or after using the product.
・If the product gets into the eyes, don't rub but rinse with water.
・Don't place the product in any place where it will be subjected to extremely high or low temperatures or direct sunlight.

DOSAGE AND ADMINISTRATION

for external use only